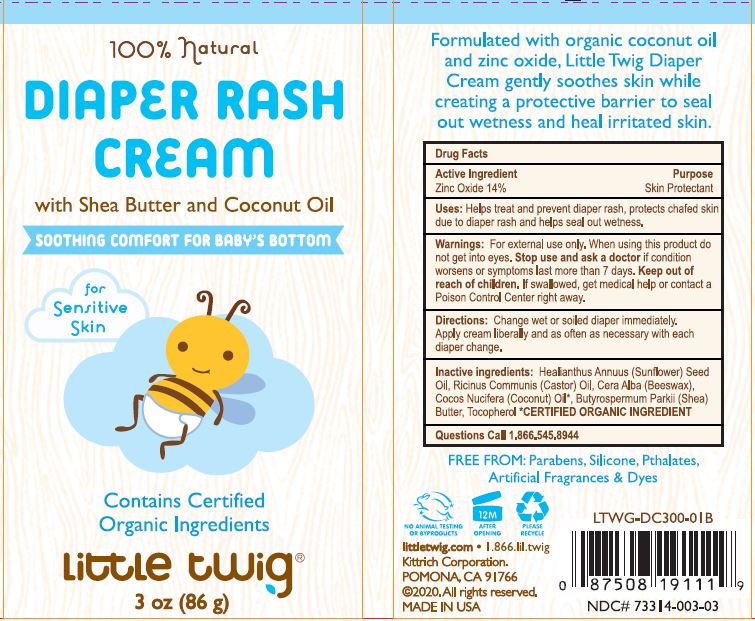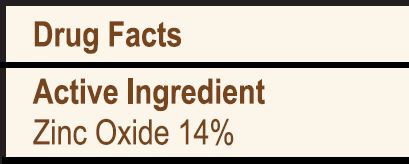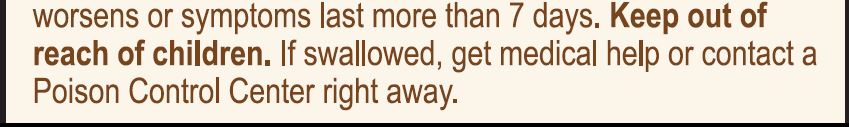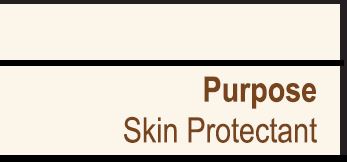 DRUG LABEL: Diaper Cream
NDC: 62932-232 | Form: LOTION
Manufacturer: Private Label Select Ltd CO
Category: otc | Type: HUMAN OTC DRUG LABEL
Date: 20201229

ACTIVE INGREDIENTS: ZINC OXIDE 14 g/100 g
INACTIVE INGREDIENTS: CASTOR OIL; SHEA BUTTER; .BETA.-TOCOPHEROL; SUNFLOWER OIL; COCONUT OIL; .ALPHA.-TOCOPHEROL, D-; JOJOBA OIL; WHITE WAX; .GAMMA.-TOCOPHEROL; .DELTA.-TOCOPHEROL

Little Twig 100% Natural Diaper Rash Cream